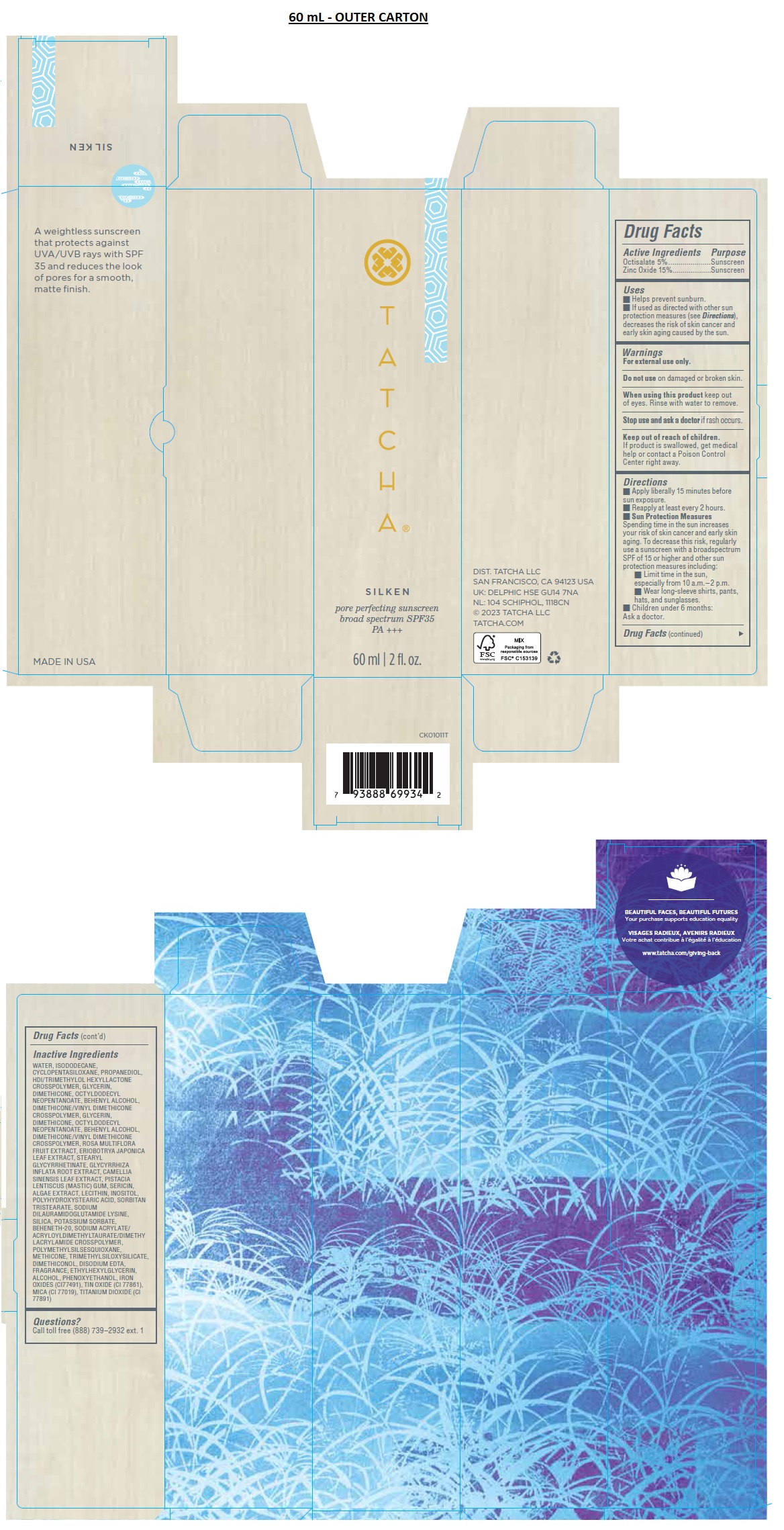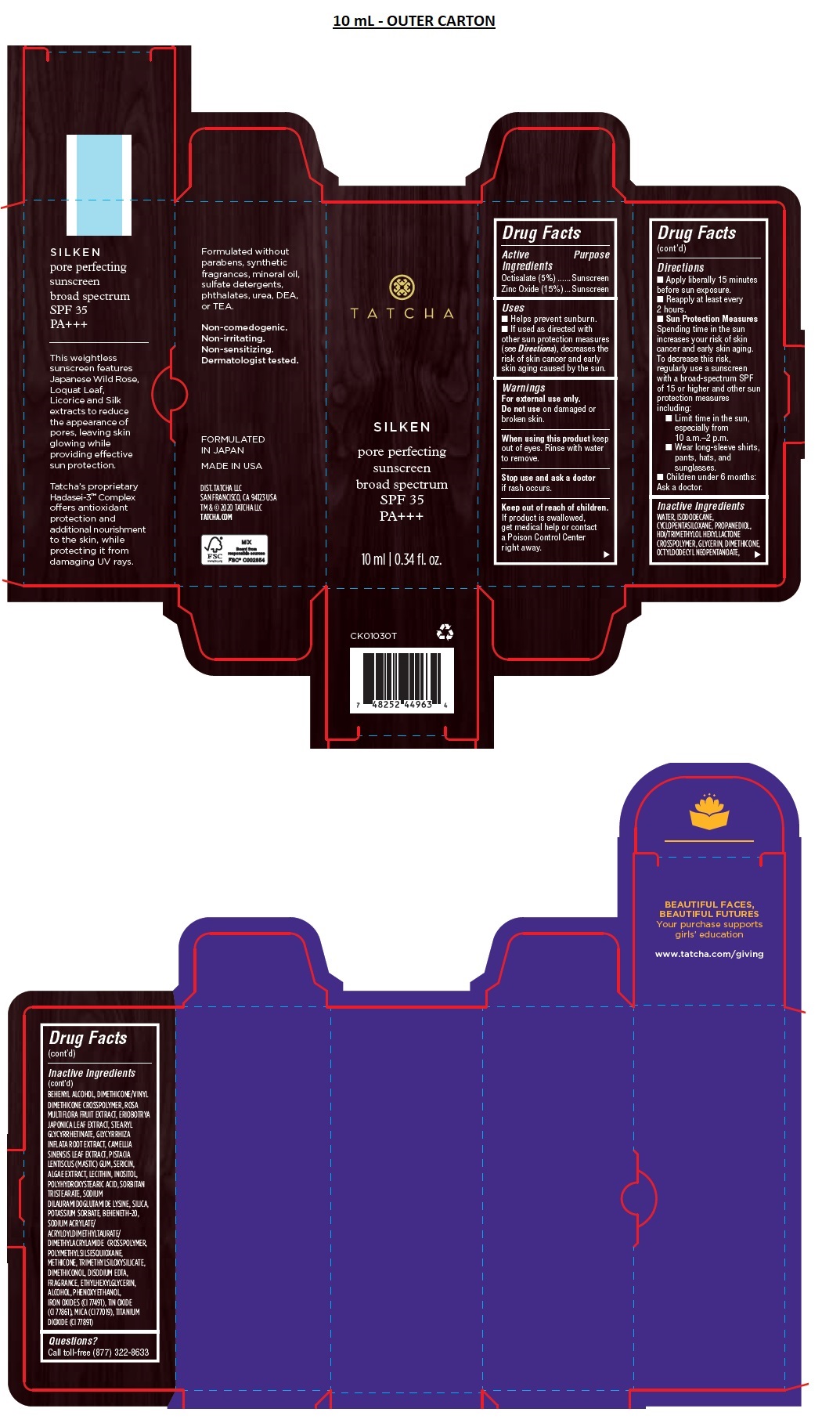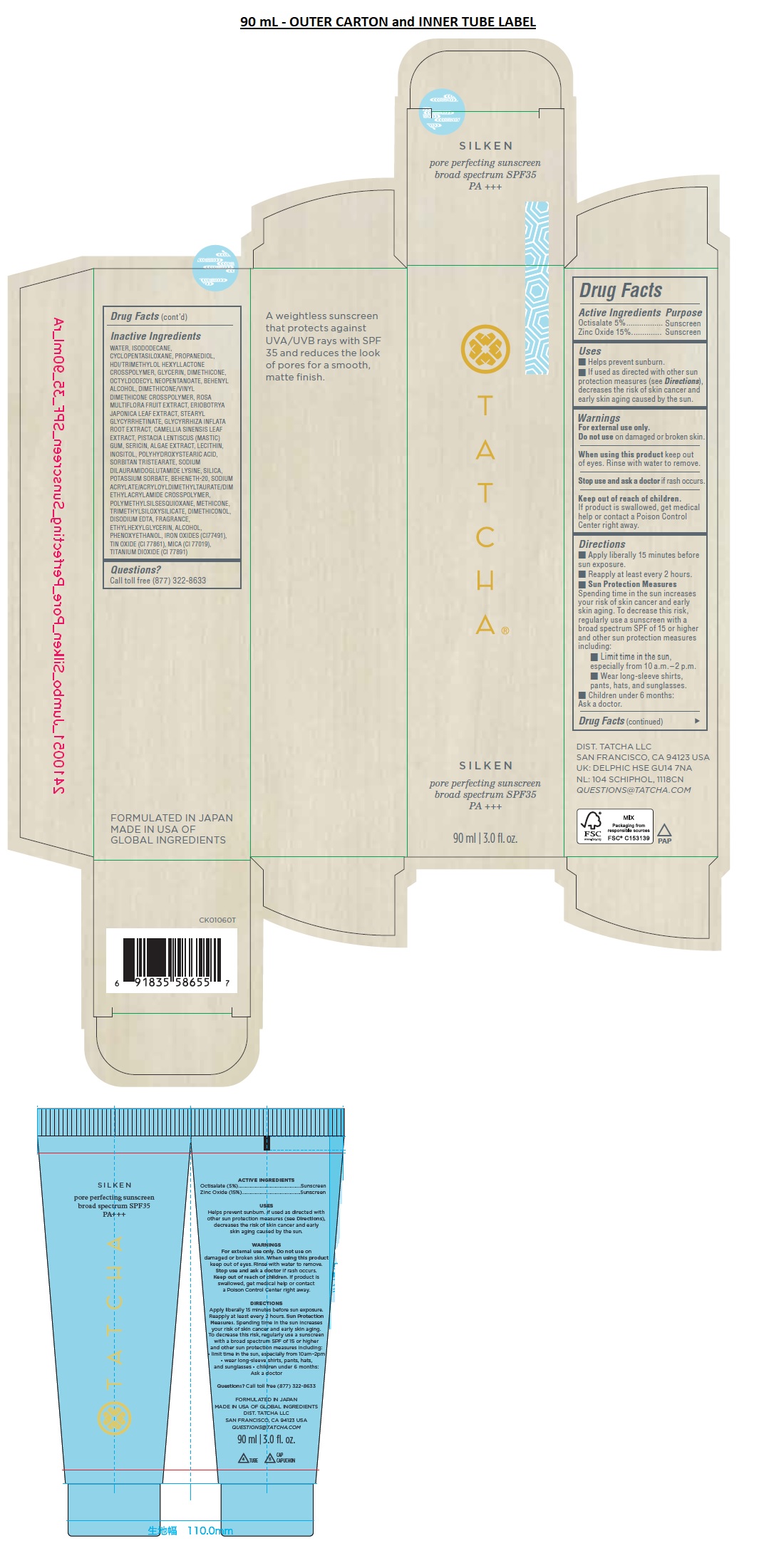 DRUG LABEL: SILKEN pore perfecting sunscreen broad spectrum SPF 35
NDC: 69417-150 | Form: LOTION
Manufacturer: TATCHA INC.
Category: otc | Type: HUMAN OTC DRUG LABEL
Date: 20250416

ACTIVE INGREDIENTS: OCTISALATE 5 g/100 mL; ZINC OXIDE 15 g/100 mL
INACTIVE INGREDIENTS: WATER; ISODODECANE; CYCLOMETHICONE 5; PROPANEDIOL; HEXAMETHYLENE DIISOCYANATE/TRIMETHYLOL HEXYLLACTONE CROSSPOLYMER; GLYCERIN; DIMETHICONE, UNSPECIFIED; OCTYLDODECYL NEOPENTANOATE; DIMETHICONE/VINYL DIMETHICONE CROSSPOLYMER (SOFT PARTICLE); ROSA MULTIFLORA FRUIT; ERIOBOTRYA JAPONICA LEAF; STEARYL GLYCYRRHETINATE; GLYCYRRHIZA INFLATA ROOT; GREEN TEA LEAF; PISTACIA LENTISCUS RESIN; SILK SERICIN; SOYBEAN LECITHIN; INOSITOL; POLYHYDROXYSTEARIC ACID (2300 MW); SORBITAN TRISTEARATE; SODIUM DILAURAMIDOGLUTAMIDE LYSINE; SILICON DIOXIDE; POTASSIUM SORBATE; BEHENETH-20; METHICONE (20 CST); EDETATE DISODIUM; ETHYLHEXYLGLYCERIN; ALCOHOL; PHENOXYETHANOL; FERRIC OXIDE RED; STANNIC OXIDE; MICA; TITANIUM DIOXIDE

SILKEN pore perfecting sunscreen broad spectrum SPF 35

Active Ingredients

Octisalate 5%

Zinc Oxide 15%

Purpose

Sunscreen

Uses

- Helps prevent sunburn.
- If used as directed with other sun protection measures (see Directions), decreases the risk of skin cancer and early skin aging caused by the sun.

Warnings

For external use only.

Do not use on damaged or broken skin.

When using this product keep out of eyes. Rinse with water to remove.

Stop use and ask a doctor if rash occurs.

Keep out of reach of children.

If product is swallowed, get medical help or contact a Poison Control Center right away.

Directions

- Apply liberally 15 minutes before sun exposure.
- Reapply at least every 2 hours.
- Sun Protection Measures
  Spending time in the sun increases your risk of skin cancer and early skin aging. To decrease this risk, regularly use a sunscreen with a broad spectrum SPF of 15 or higher and other sun protection measures including:
  • Limit time in the sun, especially from 10 a.m.–2 p.m.
  • Wear long-sleeve shirts, pants, hats, and sunglasses.
- Children under 6 months: Ask a doctor.

Inactive Ingredients

WATER, ISODODECANE, CYCLOPENTASILOXANE, PROPANEDIOL, HDI/TRIMETHYLOL HEXYLLACTONE CROSSPOLYMER, GLYCERIN, DIMETHICONE, OCTYLDODECYL NEOPENTANOATE, BEHENYL ALCOHOL, DIMETHICONE/VINYL DIMETHICONE CROSSPOLYMER, ROSA MULTIFLORA FRUIT EXTRACT, ERIOBOTRYA JAPONICA LEAF EXTRACT, STEARYL GLYCYRRHETINATE, GLYCYRRHIZA INFLATA ROOT EXTRACT, CAMELLIA SINENSIS LEAF EXTRACT, PISTACIA LENTISCUS (MASTIC) GUM, SERICIN, ALGAE EXTRACT, LECITHIN, INOSITOL, POLYHYDROXYSTEARIC ACID, SORBITAN TRISTEARATE, SODIUM DILAURAMIDOGLUTAMIDE LYSINE, SILICA, POTASSIUM SORBATE, BEHENETH-20, SODIUM ACRYLATE/ACRYLOYLDIMETHYLTAURATE/DIMETHYLACRYLAMIDE CROSSPOLYMER, POLYMETHYLSILSESQUIOXANE, METHICONE, TRIMETHYLSILOXYSILICATE, DIMETHICONOL, DISODIUM EDTA, FRAGRANCE, ETHYLHEXYLGLYCERIN, ALCOHOL, PHENOXYETHANOL, IRON OXIDES (CI77491), TIN OXIDE (CI 77861), MICA (CI 77019), TITANIUM DIOXIDE (CI 77891)

Questions?

Call toll free (888) 739-2932 ext. 1

Call toll free (877) 322-8633

PA +++

A weightless sunscreen that protects against UVA/UVB rays with SPF 35 and reduces the look of pores for a smooth, matte finish.

Formulated without parabens, synthetic fragrances, mineral oil, sulfate detergents, phthalates, urea, DEA or TEA.

Non-comedogenic.

Non-irritating.

Non-sensitizing.

Dermatologist tested.

FORMULATED IN JAPAN

MADE IN USA OF GLOBAL INGREDIENTS

DIST. TATCHA LLC

SAN FRANCISCO, CA 94123 USA

UK: DELPHIC HSE GU14 7NA

NL: 104 SCHIPHOL, 1118CN

© 2023 TATCHA LLC

QUESTIONS@TATCHA.COM

BEAUTIFUL FACES, BEAUTIFUL FUTURES

Your purchase supports education equality

www.tatcha.com/giving-back